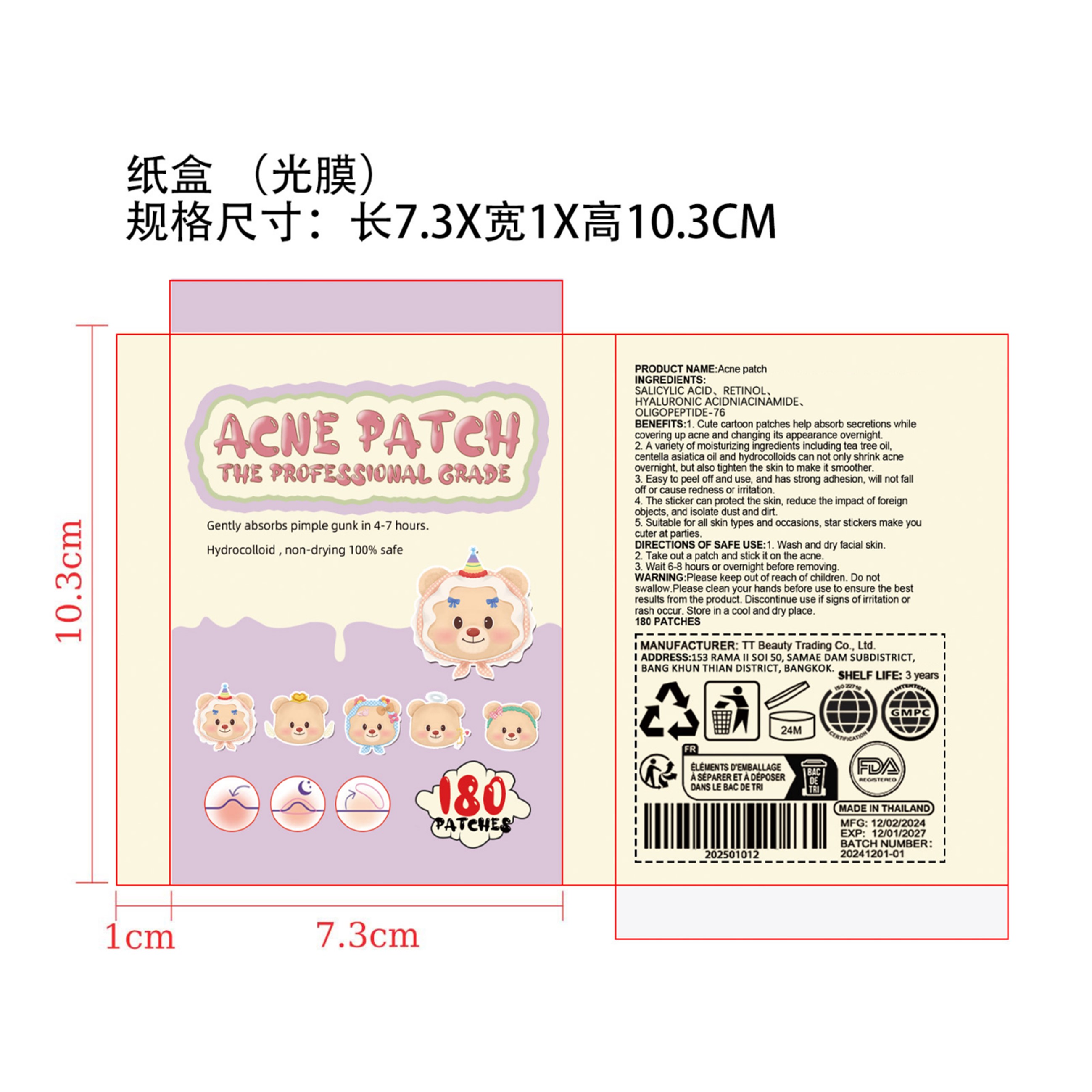 DRUG LABEL: Acne patch
NDC: 85206-001 | Form: PATCH
Manufacturer: TT Beauty Trading Co., Ltd.
Category: otc | Type: HUMAN OTC DRUG LABEL
Date: 20250205

ACTIVE INGREDIENTS: SALICYLIC ACID 0.2 g/100 g
INACTIVE INGREDIENTS: OLIGOPEPTIDE-74; NIACINAMIDE; RETINOL; HYALURONIC ACID

INGREDIENTS:

SALICYLIC ACID、RETINOL、HYALURONIC ACIDNIACINAMIDE、OLIGOPEPTIDE-76

Please keep out of reach of children.

BENEFITS:

1.Cute cartoon patches help absorb secretions whilecovering up acne and changing its appearance overnight.2. A variety of moisturizing ingredients induding tea tree oi,centella asiatica oil and hydrocolloids can not only shrink acneovernight, but also tighten the skin to make it smoother.3. Easy to peel off and use, and has strong adhesion, will not falloff or cause redness or imritation.4. The sticker can protect the skin, reduce the impact of foreignobjects, and isolate dust and dirt.5. Suitable for all skin types and occasions, star stickers make youcuter at parties.

WARNING:

Please keep out of reach of children. Do notswallow.Please clean your hands before use to ensure the bestresults from the product. Discontinue use if signs of irritation orrash occur. Store in a cool and dry place.

DIRECTIONS OF SAFE USE:

1. Wash and dry facial skin.2. Take out a patch and stick it on the acne.3. Wait 6-8 hours or ovemight before removing